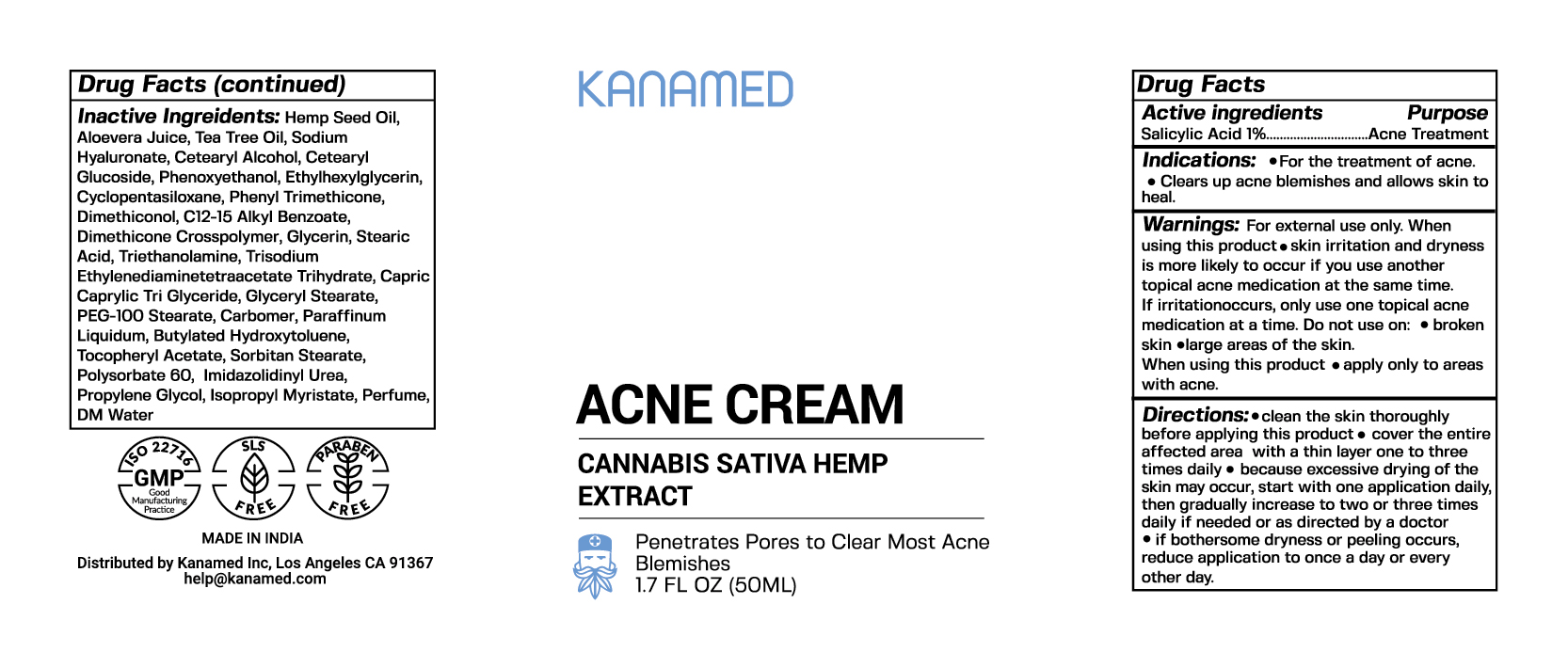 DRUG LABEL: Acne Cream
NDC: 73239-1903 | Form: CREAM
Manufacturer: Kanamed Inc.
Category: otc | Type: HUMAN OTC DRUG LABEL
Date: 20191024

ACTIVE INGREDIENTS: SALICYLIC ACID 1 mg/100 mL
INACTIVE INGREDIENTS: ALOE VERA WHOLE; HEMP; WATER 1 mg/100 mL

Acne Cream

ACTIVE INGREDIENT

SALICYLIC ACID 1%

INDICATIONS AND USAGE

Acne Treatment

INACTIVE INGREDIENT

- Hemp seed oil
- Alovera Juice
- Tea Tree Oil
- Sodium Hyaluronate
- Cetearyl Alcohol
- Cetearyl Glucoside
- Phenoxyethanol
- Ethylhexylglycerin
- Cyclopentasiloxane
- Phenyl Trimethicone
- Dimethiconol
- C12-15 Alkyl Benzoate
- Dimethicone Crosspolymer
- Glycerine
- Stearic Acid
- Triethanolamine
- Trisodium Ethylenediaminetetracetate Trihydrate,
- Glyceryl Stearate
- PEG-100 Stearate
- Carbomer
- Paraffinum Liquidum
- Butylated Hydroxytoluene
- Tocopheryl Acetate
- Sorbitan Stearate
- Polysorbate 60
- Imidazolidnyl Urea
- Propylene Glycol
- Isopropyl Myristate
- Perfume
- DM Water
- Phenyl Trimethicone

DOSAGE AND ADMINISTRATION

- Clean the skin thoroughly before applying this product
- Cover the entire affected area with a thin layer one to three times daily
- Because excessive drying of the skin may occur, start with one application daily then gradually increase to two or three times daily if needed or as directed by a doctor
- If bothersome dryness or peeling occurs reduce application to once a day or every other day

WARNINGS

- For external use only
- When using this product
  skin irritation and dryness is more likely to occur if you use another topical acne medication at the same time. If irritation occurs, only use one topical acne medication at all a time.

Do not use on broken skin or large areas of skin

When using this product apply only to areas with acne

Keep out of reach of children.

PURPOSE

Acne Treatment